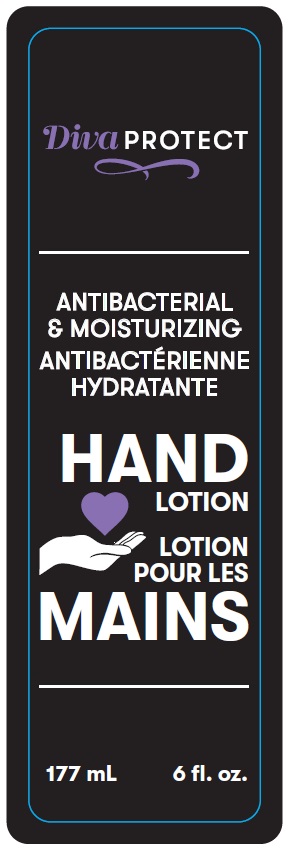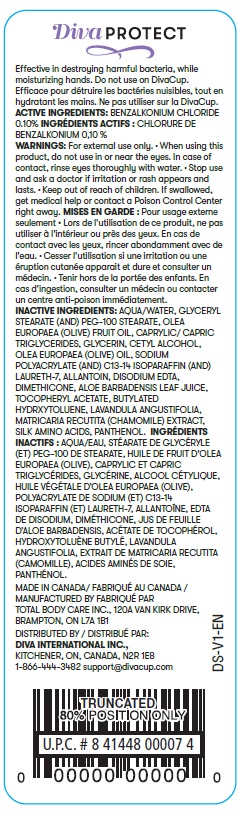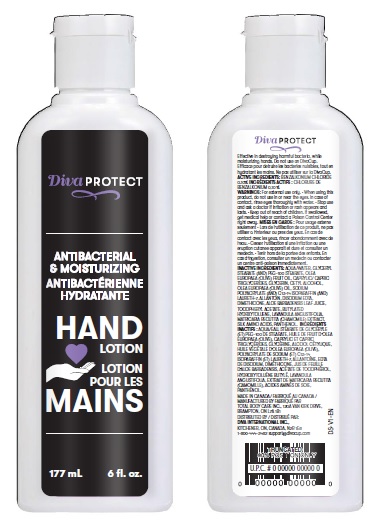 DRUG LABEL: DIVAPROTECT Hand Sanitizer
NDC: 77116-001 | Form: LIQUID
Manufacturer: Diva International Inc.
Category: otc | Type: HUMAN OTC DRUG LABEL
Date: 20200501

ACTIVE INGREDIENTS: BENZALKONIUM CHLORIDE 1 g/1000 mL
INACTIVE INGREDIENTS: WATER; GLYCERIN; CETYL ALCOHOL; MEDIUM-CHAIN TRIGLYCERIDES; EDETATE DISODIUM; GLYCERYL STEARATE/PEG-100 STEARATE; OLIVE OIL; ALLANTOIN; LAVENDER OIL; BENTONITE; DIMETHICONE; ALOE VERA LEAF; .ALPHA.-TOCOPHEROL ACETATE; CHAMOMILE; AMINO ACIDS, SILK; PANTHENOL; BUTYLATED HYDROXYTOLUENE

Active ingredient

Benzalkonium Chloride 0.10%

Uses

Effective in destroying harmful bacteria, while moisturizing hands.

Warnings

- For external use only.
- When using this product, do not use in or near the eyes. In case of contact, rinse eyes thoroughly with water.
- Stop use and ask a doctor if irritation or rash appears and lasts.

Keep out of reach of children. If swallowed, get medical help or contact a Poison Control Center right away.

Directions

- Place enough product on hands to cover all surfaces. Rub hands together until dry.
- Supervise children under 6 years of age when using this product to avoid swallowing.

Inactive ingredients

Aqua/Water, Glyceryl Stearate (and) PEG-100 Stearate, Olea Europaea (Olive) Fruit Oil, Caprylic/Capric Triglycerides, Glycerin, Cetyl alcohol, Olea Europaea (Olive) Oil, Sodium Polyacrylate (and) C13-14 Isoparaffin (and) Laureth-7, Allantoin, Disodium EDTA, Dimethicone, Aloe Barbadensis Leaf Juice, Tocopheryl Acetate, Butylated Hydrxytoluene, Lavandula Angustifolia, Matricaria Recutita (Chamomile) Extract, Silk Amino Acids, Panthenol